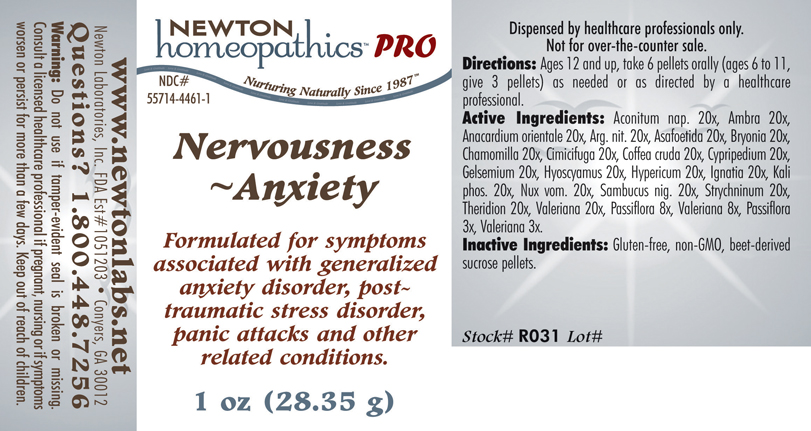 DRUG LABEL: Nervousness - Anxiety 
NDC: 55714-4461 | Form: PELLET
Manufacturer: Newton Laboratories, Inc.
Category: homeopathic | Type: HUMAN PRESCRIPTION DRUG LABEL
Date: 20110601

ACTIVE INGREDIENTS: Aconitum Napellus 20 [hp_X]/1 g; Ambergris 20 [hp_X]/1 g; Semecarpus Anacardium Juice 20 [hp_X]/1 g; Silver Nitrate 20 [hp_X]/1 g; Asafetida 20 [hp_X]/1 g; Bryonia Alba Root 20 [hp_X]/1 g; Matricaria Recutita 20 [hp_X]/1 g; Black Cohosh 20 [hp_X]/1 g; Arabica Coffee Bean 20 [hp_X]/1 g; Cypripedium Parvifolum Root 20 [hp_X]/1 g; Gelsemium Sempervirens Root 20 [hp_X]/1 g; Hyoscyamus Niger 20 [hp_X]/1 g; Hypericum Perforatum 20 [hp_X]/1 g; Strychnos Ignatii Seed 20 [hp_X]/1 g; Potassium Phosphate, Dibasic 20 [hp_X]/1 g; Strychnos Nux-vomica Seed 20 [hp_X]/1 g; Sambucus Nigra Flowering Top 20 [hp_X]/1 g; Strychnine 20 [hp_X]/1 g; Theridion Curassavicum 20 [hp_X]/1 g; Valerian 20 [hp_X]/1 g; Passiflora Incarnata Flowering Top 8 [hp_X]/1 g
INACTIVE INGREDIENTS: Sucrose

Nervousness - Anxiety

INDICATIONS & USAGE SECTION

Nervousness - Anxiety Formulated for symptoms associated with generalized anxiety disorder, post-traumatic stress disorder, panic attacks and other related conditions.

DOSAGE & ADMINISTRATION SECTION

Directions: Ages 12 and up, take 6 pellets orally (ages 6 to 11, give 3 pellets) as needed or as directed by a healthcare professional.

ACTIVE INGREDIENT SECTION

Aconitum nap. 20x, Ambra 20x, Anacardium orientale 20x, Arg. nit. 20x, Asafoetida 20x, Bryonia 20x, Chamomilla 20x, Cimicifuga 20x, Coffea cruda 20x, Cypripedium 20x, Gelsemium 20x, Hyoscyamus 20x, Hypericum 20x, Ignatia 20x, Kali phos. 20x, Nux vom. 20x, Sambucus nig. 20x, Strychninum 20x, Theridion 20x, Valeriana 20x, Passiflora 8x, Valeriana 8x, Passiflora 3x, Valeriana 3x.

PURPOSE SECTION

Formulated for symptoms associated with generalized anxiety disorder, post-traumatic stress disorder, panic attacks and other related conditions.

INACTIVE INGREDIENT SECTION

Inactive Ingredients: Gluten-free, non-GMO, beet-derived sucrose pellets.

QUESTIONS? SECTION

www.newtonlabs.net Newton Laboratories, Inc. FDA Est # 1051203 - Conyers, GA 30012
Questions? 1.800.448.7256

WARNINGS SECTION

Warning: Do not use if tamper - evident seal is broken or missing. Consult a licensed healthcare professional if pregnant, nursing or if symptoms worsen or persist for more than a few days. Keep out of reach of children.

PREGNANCY OR BREAST FEEDING SECTION

Consult a licensed healthcare professional if pregnant, nursing or if symptoms worsen or persist for more than a few days

KEEP OUT OF REACH OF CHILDREN SECTION

Keep out of reach of children